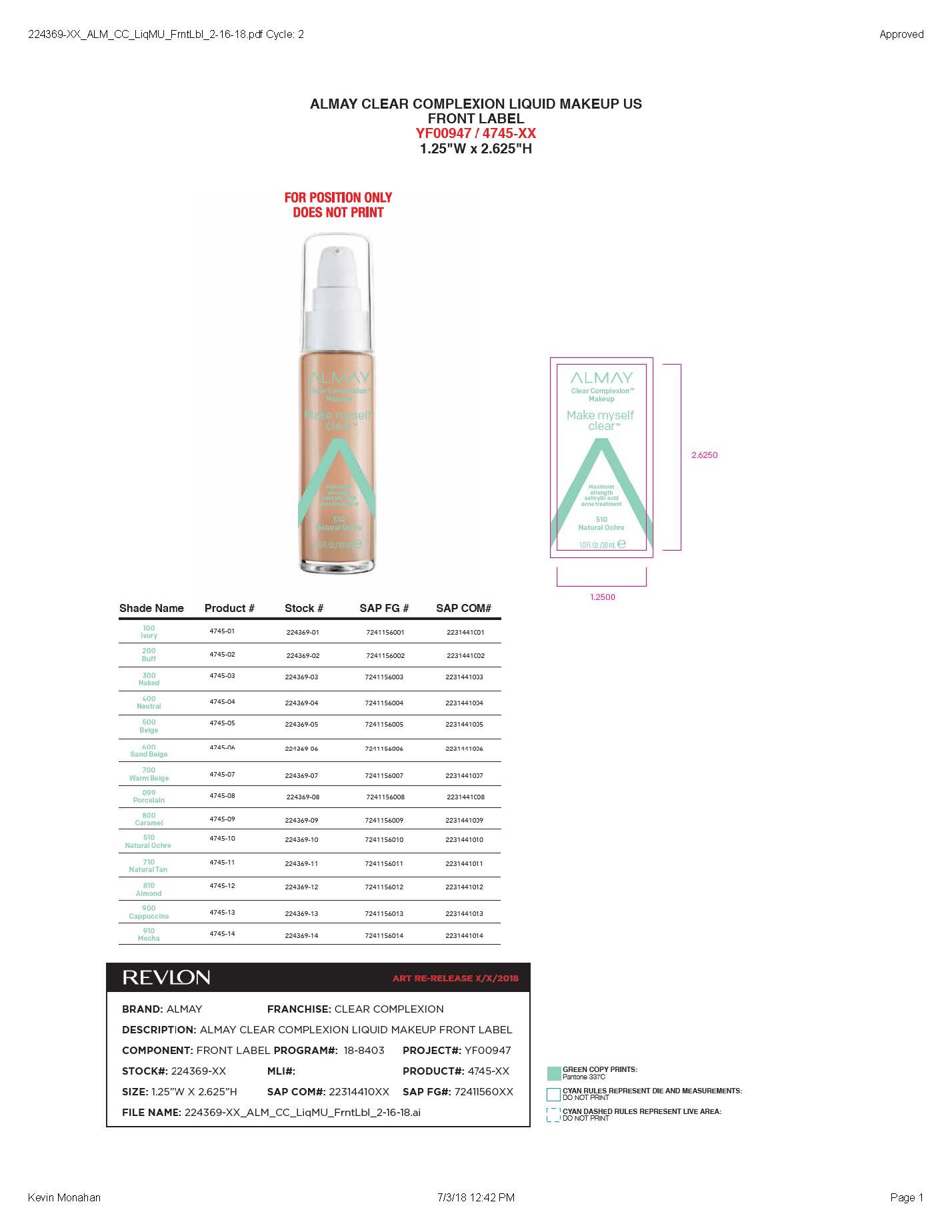 DRUG LABEL: Almay Clear Complexion Makeup
NDC: 0311-0743 | Form: LIQUID
Manufacturer: Almay
Category: otc | Type: HUMAN OTC DRUG LABEL
Date: 20241231

ACTIVE INGREDIENTS: SALICYLIC ACID 2 mg/2 mL
INACTIVE INGREDIENTS: HEXYLENE GLYCOL; TRIBEHENIN; DIMETHICONE/BIS-ISOBUTYL PPG-20 CROSSPOLYMER; METHICONE (20 CST); TRISILOXANE; TRIETHOXYCAPRYLYLSILANE; SODIUM BENZOATE; SILICA; DIPOTASSIUM GLYCYRRHIZATE; ALOE VERA LEAF; CHAMOMILE; TETRASODIUM EDTA; DIMETHICONE; CI 77491; SILICA DIMETHYL SILYLATE; EDETATE DISODIUM; MICA; ETHYLHEXYL PALMITATE; CENTAUREA CYANUS FLOWER; GLYCERIN; MALTODEXTRIN; CYCLOHEXASILOXANE; SODIUM CHLORIDE; PHENOXYETHANOL; TITANIUM DIOXIDE; NYLON-12; ISODECYL NEOPENTANOATE; PEG/PPG-18/18 DIMETHICONE; CETYL PEG/PPG-10/1 DIMETHICONE (HLB 2); WATER; BUTYLENE GLYCOL; BORON NITRIDE; TRIMETHYLSILOXYSILICATE (M/Q 0.8-1.0); ALUMINA; PANTHENOL; .ALPHA.-TOCOPHEROL ACETATE; SORBITAN SESQUIOLEATE; ETHYLPARABEN; POTASSIUM SORBATE; LECITHIN, SOYBEAN; CAPRYLHYDROXAMIC ACID; PENTAERYTHRITYL TETRA-DI-T-BUTYL HYDROXYHYDROCINNAMATE; ZINC OXIDE; PANTHENYL ETHYL ETHER; LYSOPHOSPHATIDYLCHOLINE, SOYBEAN; HYDROGENATED SOYBEAN PHOSPHATIDYLCHOLINE; CI 77492; HYDROGEN DIMETHICONE (13 CST); HYDROLYZED CORN PROTEIN (ENZYMATIC; 1500 MW); METHYLPARABEN; PHYTANTRIOL; LARICIFOMES OFFICINALIS FRUITING BODY; FILIPENDULA ULMARIA FLOWER; FERROSOFERRIC OXIDE; SODIUM HYALURONATE; PHENETHYL ALCOHOL; CAPRYLYL GLYCOL; CYCLOPENTASILOXANE

Almay Clear Complexion Liquid Makeup

ACTIVE INGREDIENT

Salicylic acid 2.0%

PURPOSE

Acne treatment

WARNINGS

For external use only

WHEN USING

Skin irritation and dryness is more likely to occur if you use another topical acne medication at the same time. If occurs only use one topical acne medication at the same time.

Avoid contact with eyes. If contact occurs, flush throughly with water.

Sensitivity test for a new user:

Apply product sparingly to one or two small affected areas during the first three days. If no discomfort occurs, follow the directions above.

KEEP OUT OF REACH OF CHILDREN

If product is swallowed, get medical help or contact a Poison Control Center right away.

Directions:

Clean skin througly before applying this product. Cover entire affected area with a thin layer one to three times daily. Because excessive drying of the skin may occur , start with one application daily, then gradually increase to two or three times daily if needed or as directed by a doctor. If bothersome dryness or peeling occurs, reduce application to once a day or every other day.

INDICATIONS AND USAGE

Acne treatment

Directions:

Clean skin througly before applying this product. Cover entire affected area with a thin layer one to three times daily. Because excessive drying of the skin may occur , start with one application daily, then gradually increase to two or three times daily if needed or as directed by a doctor. If bothersome dryness or peeling occurs, reduce application to once a day or every other day.

PACKAGE LABEL

Almay Clear COmplexion Liquid Make up